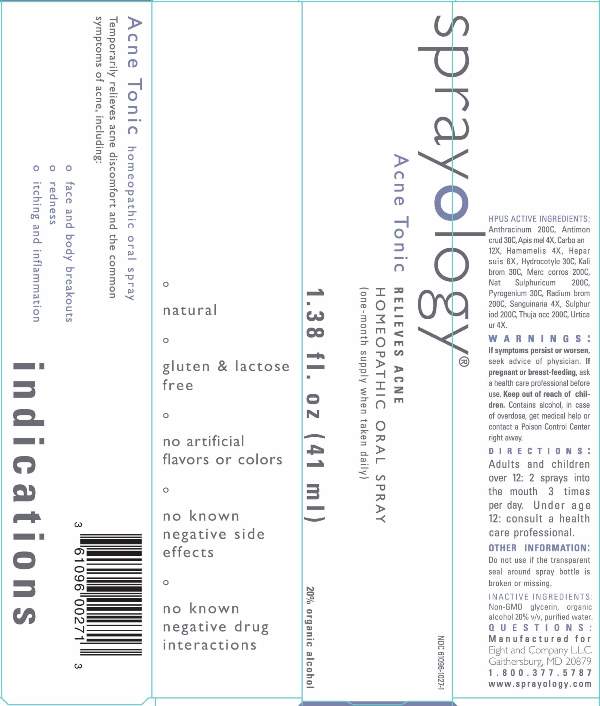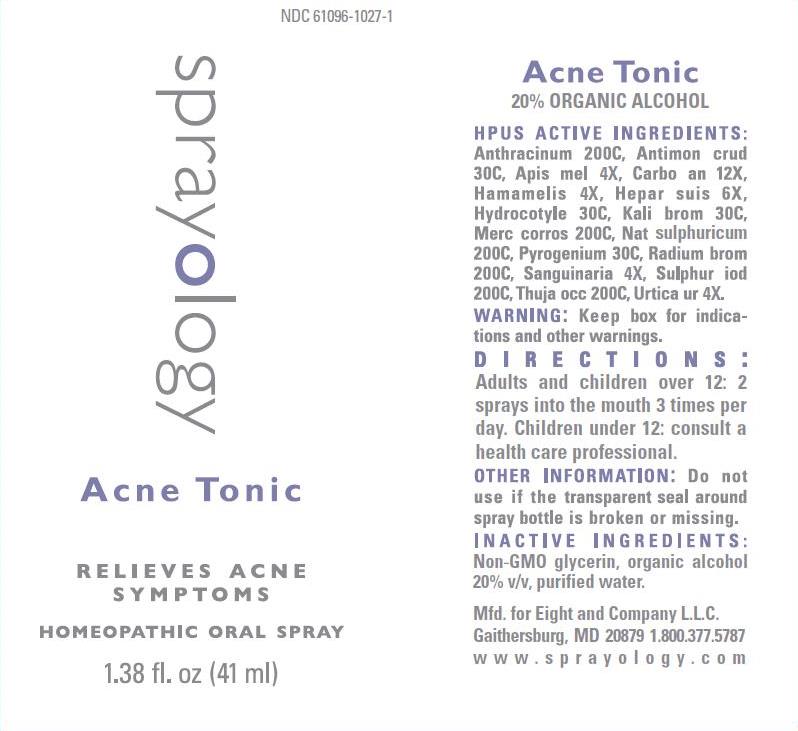 DRUG LABEL: Acne Tonic
NDC: 61096-1027 | Form: LIQUID
Manufacturer: Eight and Company L.L.C
Category: homeopathic | Type: HUMAN OTC DRUG LABEL
Date: 20251218

ACTIVE INGREDIENTS: BACILLUS ANTHRACIS IMMUNOSERUM RABBIT 200 [hp_C]/41 mL; ANTIMONY TRISULFIDE 30 [hp_C]/41 mL; APIS MELLIFERA 4 [hp_X]/41 mL; CARBO ANIMALIS 12 [hp_X]/41 mL; HAMAMELIS VIRGINIANA ROOT BARK/STEM BARK 4 [hp_X]/41 mL; PORK LIVER 6 [hp_X]/41 mL; CENTELLA ASIATICA WHOLE 30 [hp_C]/41 mL; POTASSIUM BROMIDE 30 [hp_C]/41 mL; MERCURIC CHLORIDE 200 [hp_C]/41 mL; SODIUM SULFIDE NONAHYDRATE 200 [hp_C]/41 mL; RANCID BEEF 30 [hp_C]/41 mL; RADIUM BROMIDE 200 [hp_C]/41 mL; SANGUINARIA CANADENSIS ROOT 4 [hp_X]/41 mL; SULFUR IODIDE 200 [hp_C]/41 mL; THUJA OCCIDENTALIS LEAFY TWIG 200 [hp_C]/41 mL; URTICA URENS WHOLE 4 [hp_X]/41 mL
INACTIVE INGREDIENTS: GLYCERIN; ALCOHOL; WATER

Acne Tonic

ACTIVE INGREDIENTS:

Anthracinum 200C, Antimonium crud 30C, Apis mel 4X, Carbo an 12X, Hamamelis 4X, Hepar suis 6X, Hydrocotyle 30C, Kali brom 30C, Mercurius corros 200C, Natrum sulphuricum 200C, Pyrogenium 30C, Radium bromatum 200C, Sanguinaria 4X, Sulphur iod 200C, Thuja occ 200C, Urtica ur 3X.

PURPOSE:

Temporarily relieves acne discomfort and the common symptoms of acne, including:

° Face and body breakouts
° redness
° itching and inflammation

WARNINGS:

If symptoms persist or worsen, seek advice of physician. If pregnant or breast-feeding, ask a health care professional before use. Keep out of reach of children. Contains alcohol, in case of overdose, get medical help or contact a Poison Control Center right away.

Keep out of reach of children. Contains alcohol, in case of overdose, get medical help or contact a Poison Control Center right away.

DIRECTIONS:

Adults and children over 12: 2 sprays into the mouth 3 times per day.

Children under 12: consult a health care professional.

OTHER INFORMATION:

Do not use if the transparent seal around spray bottle is broken or missing.

INDICATIONS:

Temporarily relieves acne discomfort and the common symptoms of acne, including:

° Face and body breakouts
° redness
° itching and inflammation

° natural

° gluten & lactose free

° no artificial flavors or colors

° no known negative side effects

° no known negative drug interactions

INACTIVE INGREDIENTS:

Non-GMO Glycerin, organic alcohol 20% v/v, purified water.

QUESTIONS:

Mfd. for Eight and Company L.L.C.

Gaithersburg, MD 20879 1.800.377.5787

www.sprayology.com

PACKAGE LABEL DISPLAY:

NDC 61096-1027

sprayology

Acne Tonic

RELIEVES ACNE SYMPTOMS

HOMEOPATHIC ORAL SPRAY

1.38 fl.oz (41 ml)